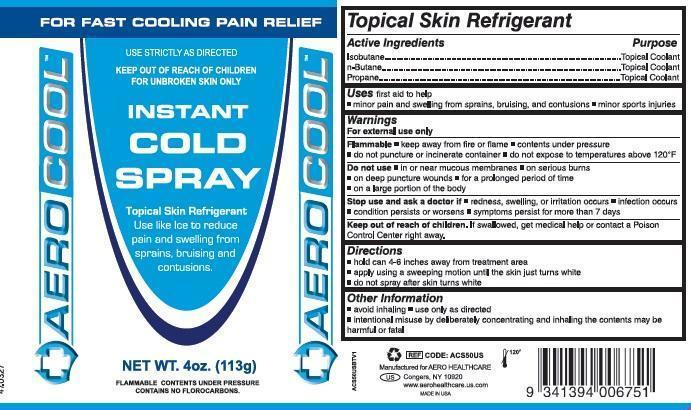 DRUG LABEL: Aerocool Cold Spray
NDC: 55305-112
Manufacturer: Aero Healthcare, LLC.
Category: other | Type: OTC MEDICAL DEVICE LABEL
Date: 20140820

Aerocool Topical Skin Refrigerant Cold Spray

Active Ingredients

Isobutane
N-Butane
Propane

Purpose

Topical Coolant
Topical Coolant
Topical Coolant

Uses

First aid to help

- minor pain and swelling from sprains, bruising, and contusion
- minor sports injuries

Warnings

For external use only

Flammable

- keep away from fire or flame
- contents under pressure
- do not puncture or incinerate container
- do not expose to temperatures above 120°F

Do not use

- in or near mucous membranes
- on serious burns
- on deep puncture wounds
- for a prolonged period of time
- on a large portion of the body

Stop use and ask a doctor if

- redness, swelling or irritation occurs
- infection occurs
- condition persists or worsens
- symptoms persist for more than 7 days

Keep out of reach of children.

If swallowed, get medical help or contact a Poison Control Center right away.

Directions

- hold can 4-6 inches away from treatment area
- apply using a sweeping motion until the skin just turns white
- do not spray after skin turns white

Other information

- avoid inhaling
- use only as directed
- intentional misuse by deliberately concentrating and inhaling the contents may be harmful or fatal